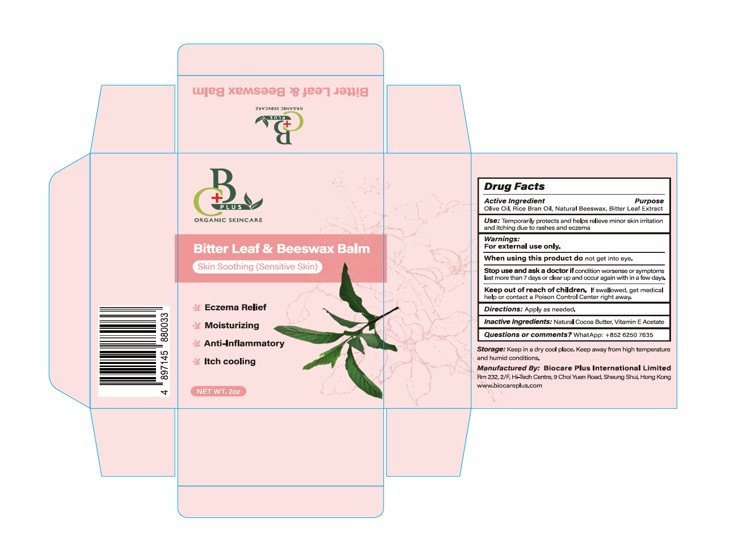 DRUG LABEL: All-Purpose Salve
NDC: 85522-002 | Form: OIL
Manufacturer: BIOCARE PLUS INTERNATIONAL LIMITED
Category: otc | Type: HUMAN OTC DRUG LABEL
Date: 20250410

ACTIVE INGREDIENTS: BEESWAX 0.17 g/1 g; VERNONIA APPENDICULATA WHOLE 0.03 g/1 g; OLIVE OIL 0.47 g/1 g; RICE BRAN OIL 0.22 g/1 g
INACTIVE INGREDIENTS: THEOBROMA CACAO (COCOA) SEED BUTTER; .ALPHA.-TOCOPHEROL ACETATE

All-Purpose Salve

ACTIVE INGREDIENT

Olive Oil
Rice Bran Oil
Natural Beeswax
Bitter Leaf Extract

PURPOSE

Moisturizing the skin

KEEP OUT OF REACH OF CHILDREN SECTION

INDICATIONS AND USAGE

Use: Temporarily protects and helps relieve minor sk¡n iritationand itching due to rashes and eczema

WARNINGS

For cxternal use only.

When using this product do not get into eye.

Stop use and ask a doctor ifcondition worscnse or syptomslast more than 7 days or clear up and occur again with in a few doys,

DOSAGE AND ADMINISTRATION

Directions: Apply as needed,

INACTIVE INGREDIENT

Natural Cocoa Butter
Vitamin E Acetate
Menthol
Natural Lemon Essentail Oil